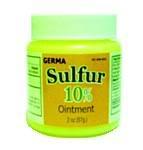 DRUG LABEL: Sulfur
NDC: 10095-007 | Form: OINTMENT
Manufacturer: World Perfumes, Inc
Category: otc | Type: HUMAN OTC DRUG LABEL
Date: 20150505

ACTIVE INGREDIENTS: SULFUR 10 g/100 g
INACTIVE INGREDIENTS: CETOSTEARYL ALCOHOL; GLYCERIN; GLYCERYL MONOSTEARATE; METHYLPARABEN; MINERAL OIL; PARAFFIN; POLYETHYLENE GLYCOL 1000; PETROLATUM; PROPYLENE GLYCOL; PROPYLPARABEN; SORBITAN MONOOLEATE; WATER

Active Ingredient Purpose

Sulfur 10% ...................... ointment

PURPOSE

Sulfur 10% ointment

Keep out of reach of children.

INDICATIONS AND USAGE

Sulfur 10% Ointment

DOSAGE AND ADMINISTRATION

Sulfur 10% Ointment

WARNINGS

Sulfur 10% Ointment

INACTIVE INGREDIENT

cetyl/stearyl alcohol, glycerin, glyceryl stearate, methylparaben, mineral oil, paraffin, polyethylenglycol, propylparaben, sorbitan oleate, water